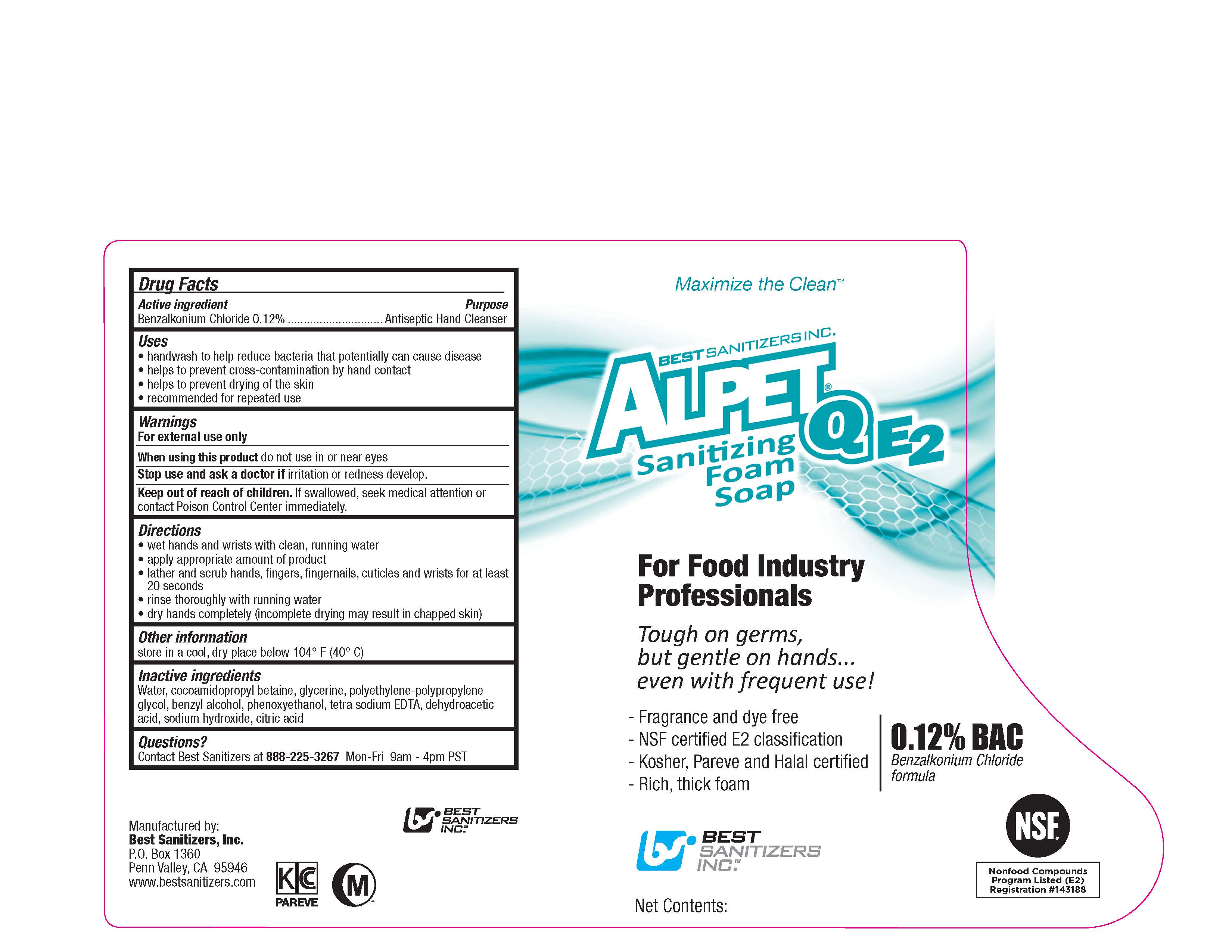 DRUG LABEL: ALPET QE2 SANITIZING FOAM
NDC: 59900-214 | Form: LIQUID
Manufacturer: Best Sanitizers, Inc.
Category: otc | Type: HUMAN OTC DRUG LABEL
Date: 20241205

ACTIVE INGREDIENTS: BENZALKONIUM CHLORIDE 1.2 mg/1 mL
INACTIVE INGREDIENTS: WATER; COCAMIDOPROPYL BETAINE; GLYCERIN; POLOXAMER 124; BENZYL ALCOHOL; PHENOXYETHANOL; EDETATE SODIUM; DEHYDROACETIC ACID; SODIUM HYDROXIDE; CITRIC ACID MONOHYDRATE

Drug Facts 59900-214

Active ingredient

Benzalkonium Chloride 0.12%

Purpose

Antiseptic Hand Cleanser

Uses

- handwash to help reduce bacteria that potentially can cause disease

- helps to prevent cross-contamination by hand contact

- helps to prevent drying of the skin

- recommended for repeated use

Warnings

For external use only

WHEN USING

When using this productdo not use in or near eyes

Stop use and ask a doctor ifirritation or redness develop.

Keep out of reach of children.

If swallowed, seek medical attention or contact a Poison Control Center immediately.

Directions

- wet hands and wrists with clean, running water

- apply appropriate amount of product

- lather and scrub hands, fingers, fingernails, cuticles and wrists for at least 20 seconds

- rinse thoroughly with running water

- dry hands completely (incomplete drying may result in chapped skin)

Other information

store in a cool, dry place below 104oF (40oC)

Inactive ingredients

Water, cocamidopropyl betaine, glycerine, polyethylene-polypropylene glycol, benzyl alcohol, phenoxyethanol, tetra sodium EDTA, dehydroacetic acid, sodium hydroxide, citric acid

Questions?

Contact Best Sanitizers at 888-225-3267Mon-Fri 9 am-4 pm PST

PACKAGE LABEL

Maximize the Clean

BEST SANITIZERS INC.

ALPET Q E2

Sanitizing Foam Soap

For Food Industry

Professionals

Tough on germs,

but gentle on hands...

even when frequent use!

Fragrance and dye free

NSF certified E2 classification

Kosher, Pareve and Halal certified

Rich, thick foam

0.12% BAC

Benzalkonium Chloride

formula

BEST

SANITIZERS

INC.

NSF

Nonfood Compounds

Program Listed (E2)

Registration Number 143188

Net Contents: